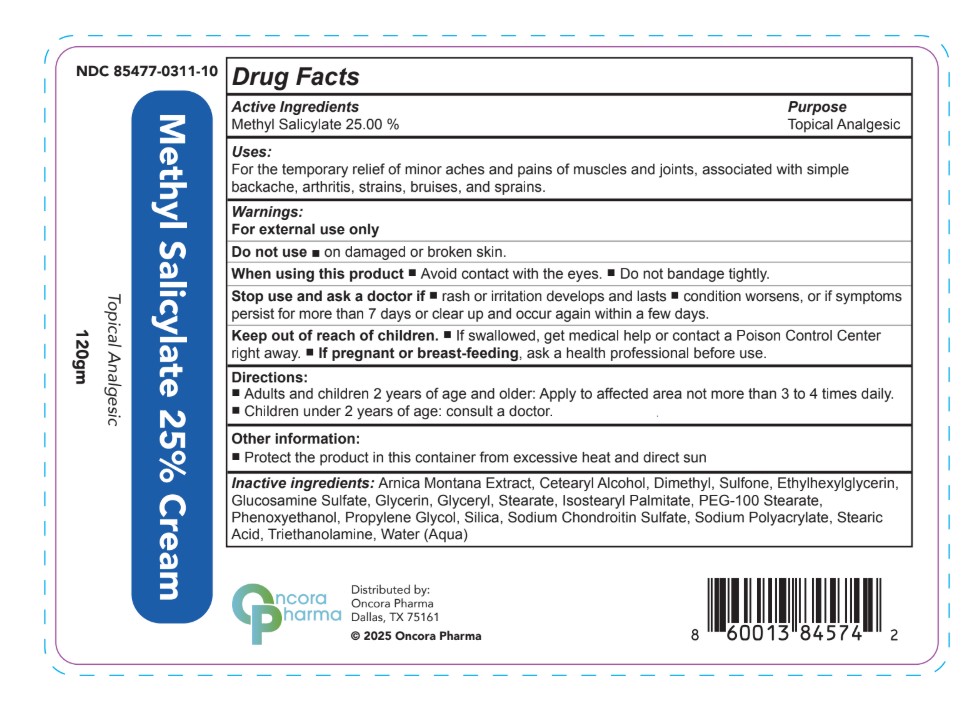 DRUG LABEL: METHYL SALICYLATE 25%
NDC: 85477-311 | Form: CREAM
Manufacturer: Oncora Pharma, LLC
Category: otc | Type: HUMAN OTC DRUG LABEL
Date: 20250813

ACTIVE INGREDIENTS: METHYL SALICYLATE 250 mg/1 g
INACTIVE INGREDIENTS: GLUCOSAMINE SULFATE; GLYCERYL STEARATE; STEARIC ACID; TRIETHANOLAMINE; PHENOXYETHANOL; ARNICA MONTANA; DIMETHYL SULFONE; ETHYLHEXYLGLYCERIN; SODIUM CHONDROITIN SULFATE (PORCINE; 5500 MW); SODIUM POLYACRYLATE (8000 MW); PEG-100 STEARATE; CETEARYL ALCOHOL; ISOSTEARYL PALMITATE; GLYCERIN; WATER; SILICON DIOXIDE

Uses

For the temporary relief of minor aches and pains of muscles and joints, associated with simpled backache, arthritis, strains, bruises and sprains.

WARNINGS

For external use only.

Do not used on damaged or broken skin.

When using this product

- Avoid contact with the eyes
- Do not bandage tightly

Stop use and ask a doctor if

- rash or irritation develops and lasts
- condition worsens
- if symptoms persist more than 7 days or clear up and occur again in a few days.

Keep out of reach of children

If swallowed get medical help or contact a Poison Control Center right away.

PREGNANCY OR BREAST FEEDING

If pregnant or breast-feeding, ask a health professional before use.

DOSAGE AND ADMINISTRATION

Adults and children 2 years of age and older: Apply to affected area not more than 3 to 4 times daily.

Children under 2 years of age, consult a doctor.

STORAGE AND HANDLING

Protect the product in this container from excessive heat and direct sun.

ACTIVE INGREDIENT

Methyl Salicylate 25%

INACTIVE INGREDIENT

Arnica Montana Extract, Cetearly Alcohol, Dimethyl Sulfone, Ethylhexylglycerin, Glucosamine Sulfate, Glycerin, Glyceryl Stearate, Isostearyl Palmitate, PEG-100 Stearate, Phenoxyethanol, Propylene Glycol, Silica, Sodium Chondroitin Sulfate, Sodium Polyacrylate, Stearic Acid, Triethanolamine, Water

Purpose

Topical Analgesic